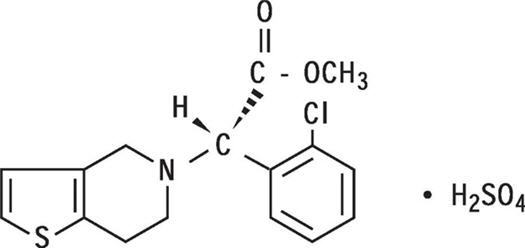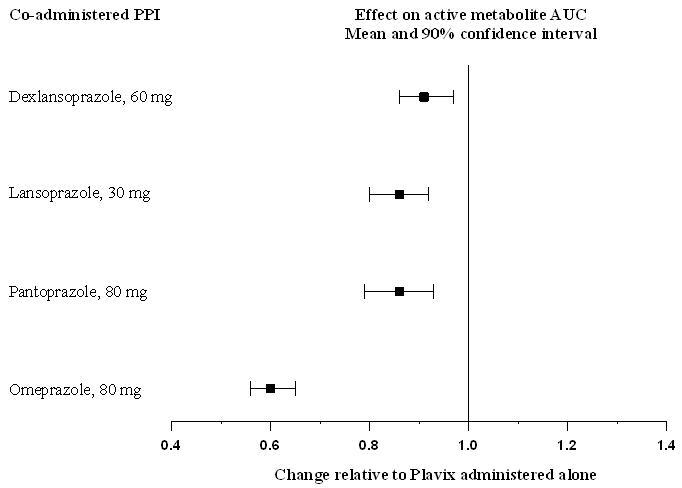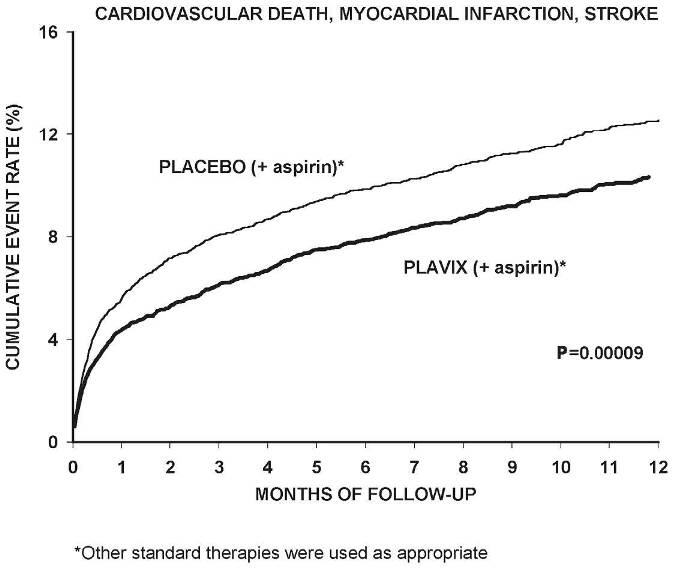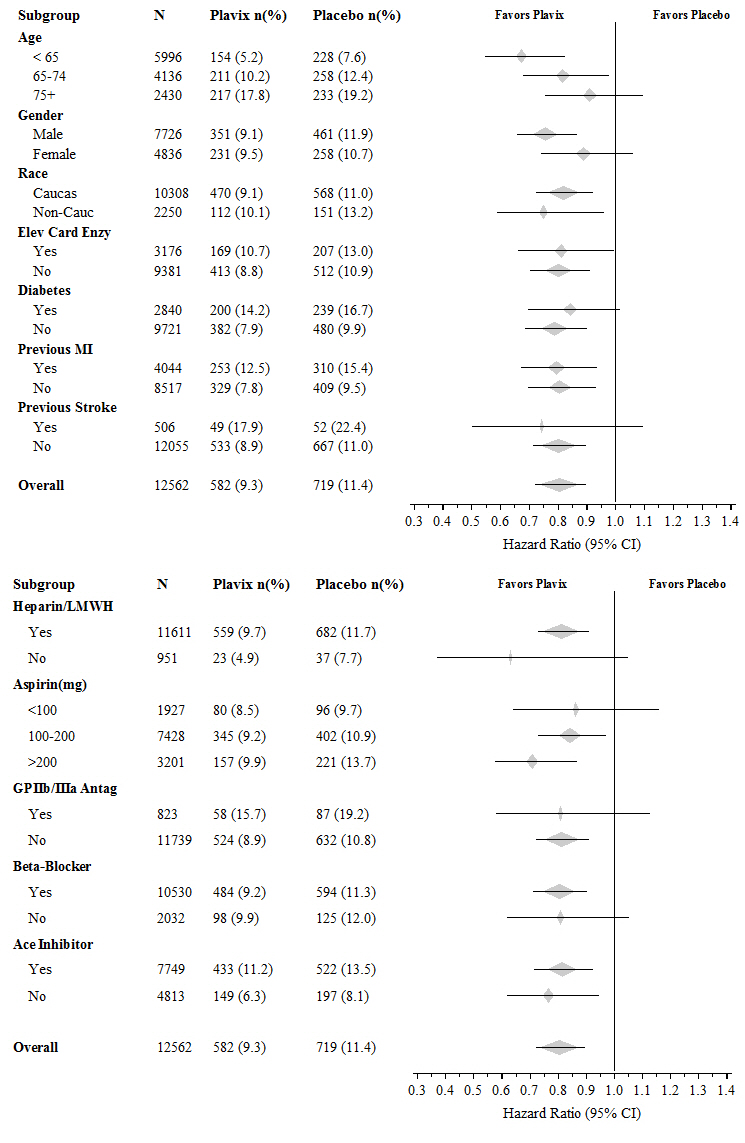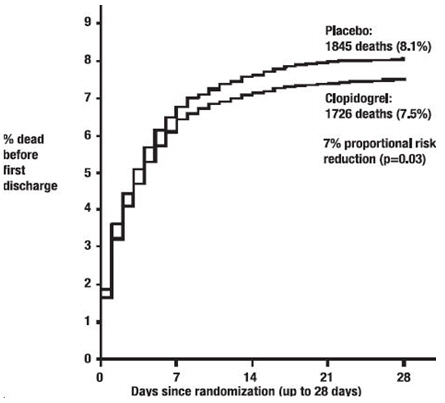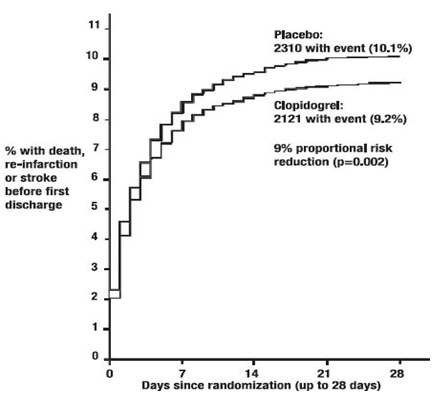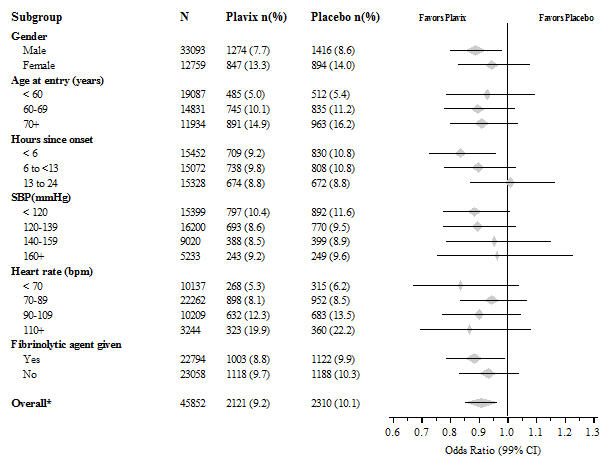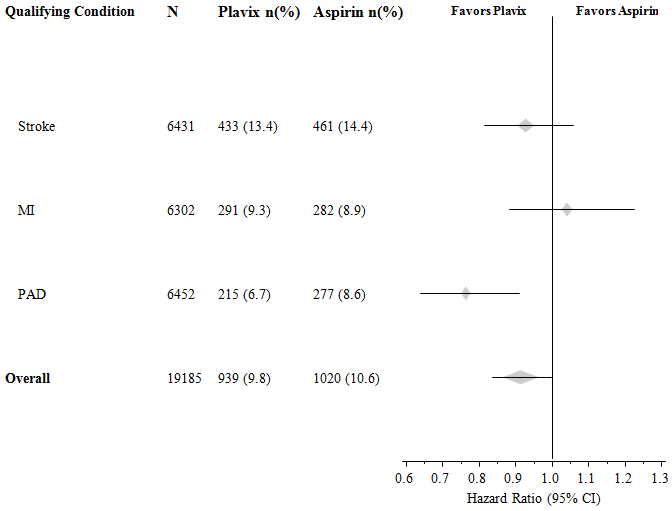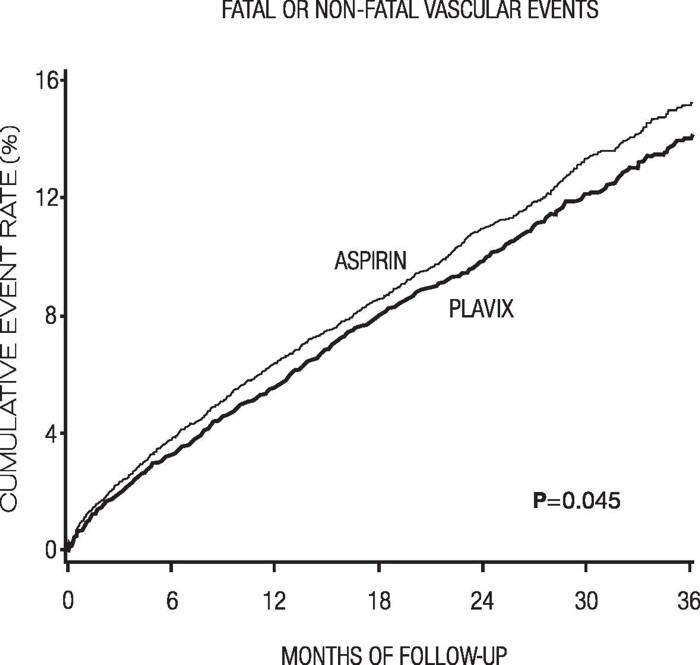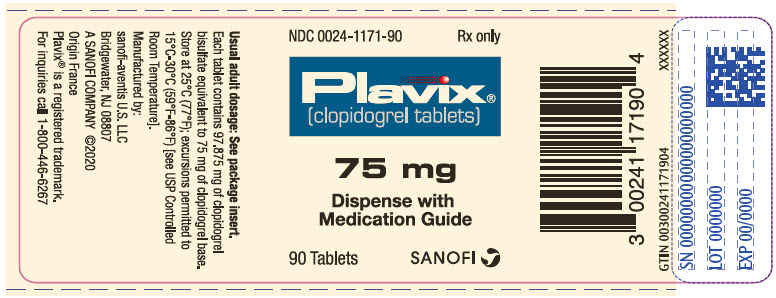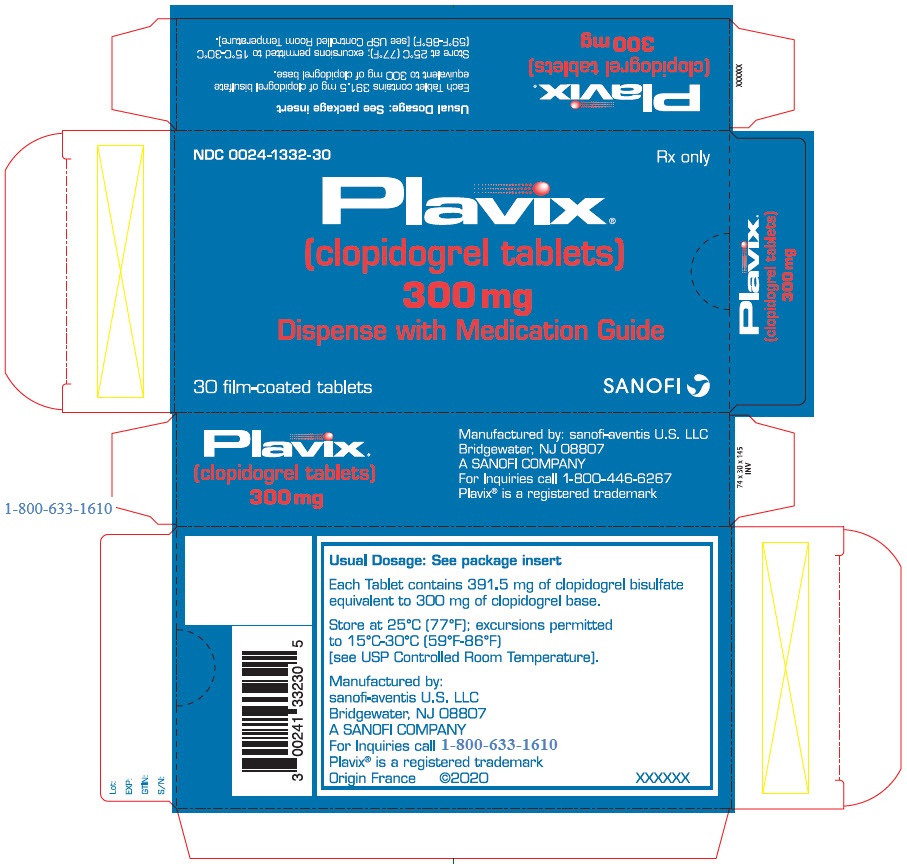 DRUG LABEL: Plavix
NDC: 0024-1171 | Form: TABLET, FILM COATED
Manufacturer: Sanofi-Aventis U.S. LLC
Category: prescription | Type: HUMAN PRESCRIPTION DRUG LABEL
Date: 20250530

ACTIVE INGREDIENTS: CLOPIDOGREL BISULFATE 75 mg/1 1
INACTIVE INGREDIENTS: CASTOR OIL; HYDROXYPROPYL CELLULOSE (1600000 WAMW); MANNITOL; MICROCRYSTALLINE CELLULOSE; POLYETHYLENE GLYCOL 6000; FERRIC OXIDE RED; LACTOSE MONOHYDRATE; TITANIUM DIOXIDE; TRIACETIN; CARNAUBA WAX

HIGHLIGHTS OF PRESCRIBING INFORMATION

These highlights do not include all the information needed to use
PLAVIX safely and effectively. See full prescribing information for
PLAVIX.
PLAVIX® (clopidogrel tablets) for oral use
Initial U.S. Approval: 1997

WARNING: DIMINISHED ANTIPLATELET EFFECT IN PATIENTS WITH TWO LOSS-OF-FUNCTION ALLELES OF THE CYP2C19 GENE

See full prescribing information for complete boxed warning.

- Effectiveness of Plavix depends on conversion to an active metabolite by the cytochrome P450 (CYP) system, principally CYP2C19. (5.1, 12.3)
- Tests are available to identify patients who are CYP2C19 poor metabolizers. (12.5)
- Consider use of another platelet P2Y12 inhibitor in patients identified as CYP2C19 poor metabolizers. (5.1)

1 INDICATIONS AND USAGE

Plavix is a P2Y12 platelet inhibitor indicated for:

- Acute coronary syndrome
  - For patients with non–ST-segment elevation ACS (unstable angina [UA]/non–ST-elevation myocardial infarction [NSTEMI]), Plavix has been shown to reduce the rate of myocardial infarction (MI) and stroke. (1.1)
  - For patients with ST-elevation myocardial infarction (STEMI), Plavix has been shown to reduce the rate of MI and stroke. (1.1)
- Recent MI, recent stroke, or established peripheral arterial disease. Plavix has been shown to reduce the rate of MI and stroke. (1.2)

2 DOSAGE AND ADMINISTRATION

- Acute coronary syndrome (2.1)
  - Initiate Plavix with a single 300 mg oral loading dose and then continue at 75 mg once daily.
  - Initiating Plavix without a loading dose will delay establishment of an antiplatelet effect by several days.
- Recent MI, recent stroke, or established peripheral arterial disease: 75 mg once daily orally without a loading dose. (2.2)

3 DOSAGE FORMS AND STRENGTHS

Film-coated tablets: 75 mg, 300 mg (3)

4 CONTRAINDICATIONS

- Active pathological bleeding, such as peptic ulcer or intracranial hemorrhage (4.1)
- Hypersensitivity to clopidogrel or any component of the product (4.2)

5 WARNINGS AND PRECAUTIONS

- CYP2C19 inhibitors: Avoid concomitant use of omeprazole or esomeprazole. (5.1)
- Bleeding: Plavix increases risk of bleeding. (5.2)
- Discontinuation: Premature discontinuation increases risk of cardiovascular events. Discontinue 5 days prior to elective surgery that has a major risk of bleeding. (5.3)
- Thrombotic thrombocytopenic purpura (TTP) has been reported. (5.4)
- Cross-reactivity among thienopyridines has been reported. (5.5)

6 ADVERSE REACTIONS

Bleeding, including life-threatening and fatal bleeding, is the most commonly reported adverse reaction. (6.1)

To report SUSPECTED ADVERSE REACTIONS, contact sanofi-aventis U.S. LLC at 1-800-633-1610 or FDA at 1-800-FDA-1088 or www.fda.gov/medwatch.

7 DRUG INTERACTIONS

- CYP2C19 inducers: Increases levels of clopidogrel active metabolite and increases platelet inhibition. (7.1)
- Opioids: Decreased exposure to clopidogrel. Consider use of parenteral antiplatelet agent. (7.3)
- Nonsteroidal anti-inflammatory drugs (NSAIDs), warfarin, selective serotonin and serotonin norepinephrine reuptake inhibitors (SSRIs, SNRIs): Increases risk of bleeding. (7.4, 7.5, 7.6)
- Other Antiplatelet Agents: Increases the risk of bleeding due to an additive effect. (7.7)
- Repaglinide (CYP2C8 substrates): Increases substrate plasma concentrations. (7.8)

FULL PRESCRIBING INFORMATION

WARNING: DIMINISHED ANTIPLATELET EFFECT IN PATIENTS WITH TWO LOSS-OF-FUNCTION ALLELES OF THE CYP2C19 GENE

The effectiveness of Plavix results from its antiplatelet activity, which is dependent on its conversion to an active metabolite by the cytochrome P450 (CYP) system, principally CYP2C19 [see Warnings and Precautions (5.1), Clinical Pharmacology (12.3)]. Plavix at recommended doses forms less of the active metabolite and so has a reduced effect on platelet activity in patients who are homozygous for nonfunctional alleles of the CYP2C19 gene, (termed "CYP2C19 poor metabolizers"). Tests are available to identify patients who are CYP2C19 poor metabolizers [see Clinical Pharmacology (12.5)]. Consider use of another platelet P2Y12 inhibitor in patients identified as CYP2C19 poor metabolizers.

1 INDICATIONS AND USAGE

1.1 Acute Coronary Syndrome (ACS)

- Plavix is indicated to reduce the rate of myocardial infarction (MI) and stroke in patients with non–ST-segment elevation ACS (unstable angina [UA]/non–ST-elevation myocardial infarction [NSTEMI]), including patients who are to be managed medically and those who are to be managed with coronary revascularization. Plavix should be administered in conjunction with aspirin.
- Plavix is indicated to reduce the rate of myocardial infarction and stroke in patients with acute ST-elevation myocardial infarction (STEMI) who are to be managed medically. Plavix should be administered in conjunction with aspirin.

1.2 Recent MI, Recent Stroke, or Established Peripheral Arterial Disease

In patients with established peripheral arterial disease or with a history of recent myocardial infarction (MI) or recent stroke Plavix is indicated to reduce the rate of MI and stroke.

2 DOSAGE AND ADMINISTRATION

2.1 Acute Coronary Syndrome

In patients who need an antiplatelet effect within hours, initiate Plavix with a single 300 mg oral loading dose and then continue at 75 mg once daily. Initiating Plavix without a loading dose will delay establishment of an antiplatelet effect by several days [see Clinical Pharmacology (12.3) and Clinical Studies (14.1)].

2.2 Recent MI, Recent Stroke, or Established Peripheral Arterial Disease

75 mg once daily orally without a loading dose [see Clinical Pharmacology (12.3) and Clinical Studies (14.2)].

3 DOSAGE FORMS AND STRENGTHS

- 75 mg tablets: Pink, round, biconvex, film-coated tablets debossed with "75" on one side and "1171" on the other
- 300 mg tablets: Pink, oblong, film-coated tablets debossed with "300" on one side and "1332" on the other

4 CONTRAINDICATIONS

4.1 Active Bleeding

Plavix is contraindicated in patients with active pathological bleeding such as peptic ulcer or intracranial hemorrhage.

4.2 Hypersensitivity

Plavix is contraindicated in patients with hypersensitivity (e.g., anaphylaxis) to clopidogrel or any component of the product [see Adverse Reactions (6.2)].

5 WARNINGS AND PRECAUTIONS

5.1 Diminished Antiplatelet Activity in Patients with Impaired CYP2C19 Function

Clopidogrel is a prodrug. Inhibition of platelet aggregation by clopidogrel is achieved through an active metabolite. The metabolism of clopidogrel to its active metabolite can be impaired by genetic variations in CYP2C19 [see Boxed Warning].

The metabolism of clopidogrel can also be impaired by drugs that inhibit CYP2C19, such as omeprazole or esomeprazole. Avoid concomitant use of Plavix with omeprazole or esomeprazole because both significantly reduce the antiplatelet activity of Plavix [see Drug Interactions (7.1)].

5.2 General Risk of Bleeding

P2Y12 inhibitors (thienopyridines), including Plavix, increase the risk of bleeding.

P2Y12 inhibitors (thienopyridines), inhibit platelet aggregation for the lifetime of the platelet (7–10 days). Because the half-life of clopidogrel's active metabolite is short, it may be possible to restore hemostasis by administering exogenous platelets; however, platelet transfusions within 4 hours of the loading dose or 2 hours of the maintenance dose may be less effective.

Use of drugs that induce the activity of CYP2C19 would be expected to result in increased drug levels of the active metabolite of clopidogrel and might potentiate the bleeding risk. As a precaution, avoid concomitant use of strong CYP2C19 inducers [see Drug Interactions (7.1) and Clinical Pharmacology (12.3)].

Risk factors for bleeding include concomitant use of other drugs that increase the risk of bleeding (e.g., anticoagulants, antiplatelet agents, and chronic use of NSAIDs) [see Drug Interactions (7.4, 7.5, 7.6, 7.7)].

5.3 Discontinuation of Plavix

Discontinuation of Plavix increases the risk of cardiovascular events. If Plavix must be temporarily discontinued (e.g., to treat bleeding or for surgery with a major risk of bleeding), restart it as soon as possible. When possible, interrupt therapy with Plavix for five days prior to such surgery. Resume Plavix as soon as hemostasis is achieved.

5.4 Thrombotic Thrombocytopenic Purpura (TTP)

TTP, sometimes fatal, has been reported following use of Plavix, sometimes after a short exposure (<2 weeks). TTP is a serious condition that requires urgent treatment including plasmapheresis (plasma exchange). It is characterized by thrombocytopenia, microangiopathic hemolytic anemia (schistocytes [fragmented RBCs] seen on peripheral smear), neurological findings, renal dysfunction, and fever [see Adverse Reactions (6.2)].

5.5 Cross-Reactivity among Thienopyridines

Hypersensitivity including rash, angioedema or hematologic reaction has been reported in patients receiving Plavix, including patients with a history of hypersensitivity or hematologic reaction to other thienopyridines [see Contraindications (4.2) and Adverse Reactions (6.2)].

6 ADVERSE REACTIONS

The following serious adverse reactions are discussed below and elsewhere in the labeling:

- Bleeding [see Warnings and Precautions (5.2)]
- Thrombotic thrombocytopenic purpura [see Warnings and Precautions (5.4)]

6.1 Clinical Trials Experience

Because clinical trials are conducted under widely varying conditions and durations of follow-up, adverse reaction rates observed in the clinical trials of a drug cannot be directly compared to rates in the clinical trials of another drug and may not reflect the rates observed in practice.

Plavix has been evaluated for safety in more than 54,000 patients, including over 21,000 patients treated for one year or more. The clinically important adverse reactions observed in trials comparing Plavix plus aspirin to placebo plus aspirin and trials comparing Plavix alone to aspirin alone are discussed below.

Bleeding

CURE

In CURE, Plavix use with aspirin was associated with an increase in major bleeding (primarily gastrointestinal and at puncture sites) compared to placebo with aspirin (see Table 1). The incidence of intracranial hemorrhage (0.1%) and fatal bleeding (0.2%) were the same in both groups. Other bleeding events that were reported more frequently in the clopidogrel group were epistaxis, hematuria, and bruise.

The overall incidence of bleeding is described in Table 1.

Table 1: CURE Incidence of Bleeding Complications (% patients)
Event | Plavix (+ aspirin) (n=6259) | Placebo (+ aspirin) (n=6303)
Major bleeding [Life-threatening and other major bleeding.] | 3.7 | 2.7
Life-threatening bleeding | 2.2 | 1.8
Fatal | 0.2 | 0.2
5 g/dL hemoglobin drop | 0.9 | 0.9
Requiring surgical intervention | 0.7 | 0.7
Hemorrhagic strokes | 0.1 | 0.1
Requiring inotropes | 0.5 | 0.5
Requiring transfusion (≥4 units) | 1.2 | 1.0
Other major bleeding | 1.6 | 1.0
Significantly disabling | 0.4 | 0.3
Intraocular bleeding with significant loss of vision | 0.05 | 0.03
Requiring 2–3 units of blood | 1.3 | 0.9
Minor bleeding [Led to interruption of study medication.] | 5.1 | 2.4

COMMIT

In COMMIT, similar rates of major bleeding were observed in the Plavix and placebo groups, both of which also received aspirin (see Table 2).

Table 2: Incidence of Bleeding Events in COMMIT (% patients)
Type of Bleeding | Plavix (+ aspirin) (n=22961) | Placebo (+ aspirin) (n=22891) | p-value
Major [Major bleeds were cerebral bleeds or noncerebral bleeds thought to have caused death or that required transfusion.] noncerebral or cerebral bleeding | 0.6 | 0.5 | 0.59
Major noncerebral | 0.4 | 0.3 | 0.48
Fatal | 0.2 | 0.2 | 0.90
Hemorrhagic stroke | 0.2 | 0.2 | 0.91
Fatal | 0.2 | 0.2 | 0.81
Other noncerebral bleeding (nonmajor) | 3.6 | 3.1 | 0.005
Any noncerebral bleeding | 3.9 | 3.4 | 0.004

CAPRIE (Plavix vs Aspirin)

In CAPRIE, gastrointestinal hemorrhage occurred at a rate of 2.0% in those taking Plavix versus 2.7% in those taking aspirin; bleeding requiring hospitalization occurred in 0.7% and 1.1%, respectively. The incidence of intracranial hemorrhage was 0.4% for Plavix compared to 0.5% for aspirin.

Other bleeding events that were reported more frequently in the Plavix group were epistaxis and hematoma.

Other Adverse Events

In CURE and CHARISMA, which compared Plavix plus aspirin to aspirin alone, there was no difference in the rate of adverse events (other than bleeding) between Plavix and placebo.

In CAPRIE, which compared Plavix to aspirin, pruritus was more frequently reported in those taking Plavix. No other difference in the rate of adverse events (other than bleeding) was reported.

6.2 Postmarketing Experience

The following adverse reactions have been identified during postapproval use of Plavix. Because these reactions are reported voluntarily from a population of an unknown size, it is not always possible to reliably estimate their frequency or establish a causal relationship to drug exposure.

Hemorrhages, including those with fatal outcome, have been reported in patients treated with Plavix.

- Blood and lymphatic system disorders: Agranulocytosis, aplastic anemia/pancytopenia, thrombotic thrombocytopenic purpura (TTP), acquired hemophilia A
- Gastrointestinal disorders: Colitis (including ulcerative or lymphocytic colitis), pancreatitis, stomatitis, gastric/duodenal ulcer, diarrhea
- General disorders and administration site condition: Fever
- Hepatobiliary disorders: Acute liver failure, hepatitis (noninfectious), abnormal liver function test
- Immune system disorders: Hypersensitivity reactions, anaphylactoid reactions, serum sickness, insulin autoimmune syndrome, which can lead to severe hypoglycemia
- Musculoskeletal, connective tissue and bone disorders: Myalgia, arthralgia, arthritis
- Nervous system disorders: Taste disorders, headache, ageusia
- Psychiatric disorders: Confusion, hallucinations
- Respiratory, thoracic and mediastinal disorders: Bronchospasm, interstitial pneumonitis, eosinophilic pneumonia
- Renal and urinary disorders: Increased creatinine levels
- Skin and subcutaneous tissue disorders: Maculopapular, erythematous or exfoliative rash, urticaria, bullous dermatitis, eczema, toxic epidermal necrolysis, Stevens-Johnson syndrome, acute generalized exanthematous pustulosis (AGEP), angioedema, drug-induced hypersensitivity syndrome, drug rash with eosinophilia and systemic symptoms (DRESS), erythema multiforme, lichen planus, generalized pruritus
- Vascular disorders: Vasculitis, hypotension

7 DRUG INTERACTIONS

7.1 CYP2C19 Inducers

Since clopidogrel is metabolized to its active metabolite partly by CYP2C19, use of drugs that induce the activity of this enzyme would be expected to result in increased drug levels of the active metabolite of clopidogrel.

Rifampin strongly induces CYP2C19 resulting to both an increase level of clopidogrel active metabolite and platelet inhibition, which in particular might potentiate the risk of bleeding. As a precaution, avoid concomitant use of strong CYP2C19 inducers [see Warnings and Precautions (5.1) and Clinical Pharmacology (12.3)].

7.2 CYP2C19 Inhibitors

Clopidogrel is metabolized to its active metabolite in part by CYP2C19. Concomitant use of drugs that inhibit the activity of this enzyme results in reduced plasma concentrations of the active metabolite of clopidogrel and a reduction in platelet inhibition [see Warnings and Precautions (5.1)].

Omeprazole or Esomeprazole

Avoid concomitant use of Plavix with omeprazole or esomeprazole. In clinical studies, omeprazole was shown to reduce significantly the antiplatelet activity of Plavix when given concomitantly or 12 hours apart. A similar reduction in antiplatelet activity was observed with esomeprazole when given concomitantly with Plavix. Dexlansoprazole, lansoprazole, and pantoprazole had less effect on the antiplatelet activity of Plavix than did omeprazole or esomeprazole [see Warnings and Precautions (5.1) and Clinical Pharmacology (12.3)].

7.3 Opioids

As with other oral P2Y12 inhibitors, coadministration of opioid agonists delay and reduce the absorption of clopidogrel, presumably because of slowed gastric emptying, resulting in reduced exposure to its metabolites [see Clinical Pharmacology (12.3)]. Consider the use of a parenteral antiplatelet agent in acute coronary syndrome patients requiring coadministration of morphine or other opioid agonists.

7.4 Nonsteroidal Anti-inflammatory Drugs (NSAIDs)

Coadministration of Plavix and NSAIDs increases the risk of gastrointestinal bleeding.

7.5 Warfarin (CYP2C9 Substrates)

Although the administration of clopidogrel 75 mg per day did not modify the pharmacokinetics of S-warfarin (a CYP2C9 substrate) or INR in patients receiving long-term warfarin therapy, coadministration of Plavix with warfarin increases the risk of bleeding because of independent effects on hemostasis.

However, at high concentrations in vitro, clopidogrel inhibits CYP2C9.

7.6 SSRIs and SNRIs

Since selective serotonin reuptake inhibitors (SSRIs) and serotonin norepinephrine reuptake inhibitors (SNRIs) affect platelet activation, the concomitant administration of SSRIs and SNRIs with clopidogrel may increase the risk of bleeding.

7.7 Other Antiplatelet Agents

Coadministration of antiplatelet agents increase the risk of bleeding due to an additive effect. Promptly evaluate any signs or symptoms of blood loss if patients are treated concomitantly with other antiplatelet agents [see Warnings and Precautions (5.2)].

7.8 Repaglinide (CYP2C8 Substrates)

The acyl-β-glucuronide metabolite of clopidogrel is a strong inhibitor of CYP2C8. Plavix can increase the systemic exposure to drugs that are primarily cleared by CYP2C8, thereby needing dose adjustment and appropriate monitoring.

Plavix increased repaglinide exposures by 3.9-fold to 5.1-fold [see Clinical Pharmacology (12.3)]. Avoid concomitant use of repaglinide with Plavix. If concomitant use cannot be avoided, initiate repaglinide at 0.5 mg before each meal and do not exceed a total daily dose of 4 mg. Increased frequency of glucose monitoring may be required during concomitant use.

8 USE IN SPECIFIC POPULATIONS

8.1 Pregnancy

Risk Summary

Available data from cases reported in published literature and postmarketing surveillance with clopidogrel use in pregnant women have not identified any drug-associated risks for major birth defects or miscarriage [see Data]. There are risks to the pregnant woman and fetus associated with myocardial infarction and stroke [see Clinical Considerations]. No evidence of fetotoxicity was observed when clopidogrel was administered to pregnant rats and rabbits during organogenesis at doses corresponding to 65 and 78 times the recommended daily human dose [see Data].

The estimated background risk of major birth defects and miscarriage for the indicated populations is unknown. All pregnancies have a background risk of birth defects, loss, or other adverse outcomes. In the U.S. general population, the estimated background risk of major birth defects and miscarriage in clinically recognized pregnancies is 2% to 4% and 15% to 20%, respectively.

Clinical Considerations

Disease-associated maternal and/or embryo/fetal risk

Myocardial infarction and stroke are medical emergencies. Therapy for the pregnant woman should not be withheld because of potential concerns regarding the effects of clopidogrel on the fetus.

Labor or delivery

Clopidogrel use during labor or delivery will increase the risk of maternal bleeding and hemorrhage. Avoid neuraxial blockade during clopidogrel use because of the risk of spinal hematoma. When possible, discontinue clopidogrel 5 to 7 days prior to labor, delivery, or neuraxial blockade.

Data

Human data

The available data from published case reports over two decades of postmarketing use have not identified an association with clopidogrel use in pregnancy and major birth defects, miscarriage, or adverse fetal outcomes.

Animal data

Embryo-fetal developmental toxicology studies were performed in pregnant rats and rabbits with doses up to 500 and 300 mg/kg/day, respectively, administered during organogenesis. These doses, corresponding to 65 and 78 times the recommended daily human dose, respectively, on a mg/m^2 basis, revealed no evidence of impaired fertility or fetotoxicity due to clopidogrel.

8.2 Lactation

Risk Summary

There are no data on the presence of clopidogrel in human milk or the effects on milk production. No adverse effects on breastfed infants have been observed with maternal clopidogrel use during lactation in a small number of postmarketing cases. Studies in rats have shown that clopidogrel and/or its metabolites are present in the milk. When a drug is present in animal milk, it is likely that the drug will be present in human milk. The developmental and health benefits of breastfeeding should be considered along with mother's clinical need for Plavix and any potential adverse effects on the breastfed infant from Plavix or from underlying maternal condition.

8.4 Pediatric Use

Safety and effectiveness in pediatric populations have not been established.

A randomized, placebo-controlled trial (CLARINET) did not demonstrate a clinical benefit of clopidogrel in neonates and infants with cyanotic congenital heart disease palliated with a systemic-to-pulmonary arterial shunt. Possible factors contributing to this outcome were the dose of clopidogrel, the concomitant administration of aspirin, and the late initiation of therapy following shunt palliation. It cannot be ruled out that a trial with a different design would demonstrate a clinical benefit in this patient population.

8.5 Geriatric Use

Of the total number of subjects in the CAPRIE and CURE controlled clinical studies, approximately 50% of patients treated with Plavix were 65 years of age and older, and 15% were 75 years and older. In COMMIT, approximately 58% of the patients treated with Plavix were 60 years and older, 26% of whom were 70 years and older.

The observed risk of bleeding events with Plavix plus aspirin versus placebo plus aspirin by age category is provided in Table 1 and Table 2 for the CURE and COMMIT trials, respectively [see Adverse Reactions (6.1)]. No dosage adjustment is necessary in elderly patients.

8.6 Renal Impairment

Experience is limited in patients with severe and moderate renal impairment [see Clinical Pharmacology (12.2)].

8.7 Hepatic Impairment

No dosage adjustment is necessary in patients with hepatic impairment [see Clinical Pharmacology (12.2)].

10 OVERDOSAGE

Platelet inhibition by Plavix is irreversible and will last for the life of the platelet. Overdose following clopidogrel administration may result in bleeding complications. A single oral dose of clopidogrel at 1500 or 2000 mg/kg was lethal to mice and to rats and at 3000 mg/kg to baboons. Symptoms of acute toxicity were vomiting, prostration, difficult breathing, and gastrointestinal hemorrhage in animals.

Based on biological plausibility, platelet transfusion may restore clotting ability.

11 DESCRIPTION

Plavix (clopidogrel tablets) is a thienopyridine class inhibitor of P2Y12 ADP platelet receptors. Chemically it is methyl (+)-(S)-α-(2-chlorophenyl)-6,7-dihydrothieno[3,2-c]pyridine-5(4H)-acetate sulfate (1:1). The empirical formula of clopidogrel bisulfate is C16H16ClNO2S•H2SO4 and its molecular weight is 419.9.

The structural formula is as follows:

Clopidogrel bisulfate is a white to off-white powder. It is practically insoluble in water at neutral pH but freely soluble at pH 1. It also dissolves freely in methanol, dissolves sparingly in methylene chloride, and is practically insoluble in ethyl ether. It has a specific optical rotation of about +56°.

Plavix for oral administration is provided as either pink, round, biconvex, debossed, film-coated tablets containing 97.875 mg of clopidogrel bisulfate which is the molar equivalent of 75 mg of clopidogrel base or pink, oblong, debossed, film-coated tablets containing 391.5 mg of clopidogrel bisulfate which is the molar equivalent of 300 mg of clopidogrel base.

Each tablet contains hydrogenated castor oil, hydroxypropyl cellulose, mannitol, microcrystalline cellulose, and polyethylene glycol 6000 as inactive ingredients. The pink film coating contains ferric oxide, hypromellose 2910, lactose monohydrate, titanium dioxide, and triacetin. The tablets are polished with Carnauba wax.

12 CLINICAL PHARMACOLOGY

12.1 Mechanism of Action

Clopidogrel is an inhibitor of platelet activation and aggregation through the irreversible binding of its active metabolite to the P2Y12 class of ADP receptors on platelets.

12.2 Pharmacodynamics

Clopidogrel must be metabolized by CYP450 enzymes to produce the active metabolite that inhibits platelet aggregation. The active metabolite of clopidogrel selectively inhibits the binding of adenosine diphosphate (ADP) to its platelet P2Y12 receptor and the subsequent ADP-mediated activation of the glycoprotein GPIIb/IIIa complex, thereby inhibiting platelet aggregation. This action is irreversible. Consequently, platelets exposed to clopidogrel's active metabolite are affected for the remainder of their lifespan (about 7 to 10 days). Platelet aggregation induced by agonists other than ADP is also inhibited by blocking the amplification of platelet activation by released ADP.

Dose-dependent inhibition of platelet aggregation can be seen 2 hours after single oral doses of Plavix. Repeated doses of 75 mg Plavix per day inhibit ADP-induced platelet aggregation on the first day, and inhibition reaches steady state between Day 3 and Day 7. At steady state, the average inhibition level observed with a dose of 75 mg Plavix per day was between 40% and 60%. Platelet aggregation and bleeding time gradually return to baseline values after treatment is discontinued, generally in about 5 days.

Geriatric Patients

Elderly (≥75 years) and young healthy subjects had similar effects on platelet aggregation.

Renally Impaired Patients

After repeated doses of 75 mg Plavix per day, patients with severe renal impairment (creatinine clearance from 5 to 15 mL/min) and moderate renal impairment (creatinine clearance from 30 to 60 mL/min) showed low (25%) inhibition of ADP-induced platelet aggregation.

Hepatically Impaired Patients

After repeated doses of 75 mg Plavix per day for 10 days in patients with severe hepatic impairment, inhibition of ADP-induced platelet aggregation was similar to that observed in healthy subjects.

Gender

In a small study comparing men and women, less inhibition of ADP-induced platelet aggregation was observed in women.

12.3 Pharmacokinetics

Clopidogrel is a prodrug and is metabolized to a pharmacologically active metabolite and inactive metabolites.

Absorption

After single and repeated oral doses of 75 mg per day, clopidogrel is rapidly absorbed. Absorption is at least 50%, based on urinary excretion of clopidogrel metabolites.

Effect of food

Plavix can be administered with or without food. In a study in healthy male subjects when Plavix 75 mg per day was given with a standard breakfast, mean inhibition of ADP-induced platelet aggregation was reduced by less than 9%. The active metabolite AUC0–24 was unchanged in the presence of food, while there was a 57% decrease in active metabolite Cmax. Similar results were observed when a Plavix 300 mg loading dose was administered with a high-fat breakfast.

Metabolism

Clopidogrel is extensively metabolized by two main metabolic pathways: one mediated by esterases and leading to hydrolysis into an inactive carboxylic acid derivative (85% of circulating metabolites) and one mediated by multiple cytochrome P450 enzymes. Cytochromes first oxidize clopidogrel to a 2-oxo-clopidogrel intermediate metabolite. Subsequent metabolism of the 2-oxo-clopidogrel intermediate metabolite results in formation of the active metabolite, a thiol derivative of clopidogrel. The active metabolite is formed mostly by CYP2C19 with contributions from several other CYP enzymes, including CYP1A2, CYP2B6 and CYP3A. The active thiol metabolite binds rapidly and irreversibly to platelet receptors, thus inhibiting platelet aggregation for the lifespan of the platelet.

The Cmax of the active metabolite is twice as high following a single 300 mg clopidogrel loading dose as it is after four days of 75 mg maintenance dose. Cmax occurs approximately 30 to 60 minutes after dosing. In the 75 to 300 mg dose range, the pharmacokinetics of the active metabolite deviates from dose proportionality: 4-fold the dose results in 2.0-fold and 2.7-fold the Cmax and AUC, respectively.

Elimination

Following an oral dose of ^14C-labeled clopidogrel in humans, approximately 50% of total radioactivity was excreted in urine and approximately 46% in feces over the 5 days post dosing. After a single, oral dose of 75 mg, clopidogrel has a half-life of approximately 6 hours. The half-life of the active metabolite is about 30 minutes.

Drug Interactions

Effect of other drugs on Plavix

Clopidogrel is metabolized to its active metabolite in part by CYP2C19.

CYP2C19 inducers

Concomitant use of strong inducers of CYP2C19 results in increased plasma concentration of the active metabolite of clopidogrel and an increase in platelet inhibition.

Rifampin: Coadministration of rifampin 300 mg twice daily for 7 days with 600 mg loading dose of clopidogrel in healthy adults increased the mean AUC and Cmax of clopidogrel's thiol metabolites by 3.8-fold. Mean inhibition of platelet aggregation at 4 hours post dose was 34% higher in the presence of rifampin compared to clopidogrel administered alone.

CYP2C19 inhibitors

Concomitant use of certain inhibitors of this enzyme results in reduced plasma concentrations of the active metabolite of clopidogrel and a reduction in platelet inhibition.

Proton pump inhibitors (PPI)

The effect of proton pump inhibitors (PPI) on the systemic exposure to the clopidogrel active metabolite following multiple doses of Plavix 75 mg evaluated in dedicated drug interaction studies is presented in Figure 1.

Figure 1: Exposure to Clopidogrel Active Metabolite Following Multiple Doses of Plavix 75 mg Alone or with Proton Pump Inhibitors (PPIs)

Pharmacodynamic and pharmacokinetic parameters measured in these studies showed that the interaction was highest with omeprazole and least with dexlansoprazole.

Opioids

Coadministration of 5 mg intravenous morphine with 600 mg loading dose of clopidogrel in healthy adults decreased the AUC and Cmax of clopidogrel's thiol metabolites by 34%. Mean platelet aggregation was higher up to 2 to 4 hours with morphine coadministration.

Effect of Plavix on other drugs

In vitro studies have shown that the glucuronide metabolite of clopidogrel is a strong inhibitor of CYP2C8. Concomitant administration of repaglinide with Plavix increased the systemic exposure to repaglinide (AUC0–∞) by 5.1-fold following the loading dose (300 mg) and by 3.9-fold on day 3 of the maintenance dose (75 mg) of Plavix [see Drug Interactions (7.6)].

12.5 Pharmacogenomics

CYP2C19 is involved in the formation of both the active metabolite and the 2-oxo-clopidogrel intermediate metabolite. Clopidogrel active metabolite pharmacokinetics and antiplatelet effects, as measured by ex vivo platelet aggregation assays, differ according to CYP2C19 genotype. Patients who are homozygous for nonfunctional alleles of the CYP2C19 gene are termed "CYP2C19 poor metabolizers." Approximately 2% of White and 4% of Black patients are poor metabolizers; the prevalence of poor metabolism is higher in Asian patients (e.g., 14% of Chinese). Tests are available to identify patients who are CYP2C19 poor metabolizers.

A crossover study in 40 healthy subjects, 10 each in the four CYP2C19 metabolizer groups, evaluated pharmacokinetic and antiplatelet responses using 300 mg followed by 75 mg per day and 600 mg followed by 150 mg per day, each for a total of 5 days. Decreased active metabolite exposure and diminished inhibition of platelet aggregation were observed in the poor metabolizers as compared to the other groups.

Table 3: Active Metabolite Pharmacokinetics and Antiplatelet Responses by CYP2C19 Metabolizer Status
 | Dose | Poor (n=10) | Intermediate [Intermediate metabolizers have one but not two nonfunctional alleles.] (n=10) | Normal (n=10) | Ultrarapid [Ultrarapid metabolizers have at least one gain-of-function allele.] (n=10)
Cmax (ng/mL) | 300 mg (24 h) | 11 (4) | 23 (11) | 32 (21) | 24 (10)
 | 600 mg (24 h) | 17 (6) | 39 (23) | 44 (27) | 36 (13)
 | 75 mg (Day 5) | 4 (1) | 12 (5) | 13 (7) | 12 (6)
 | 150 mg (Day 5) | 7 (2) | 18 (7) | 19 (5) | 16 (9)
IPA (%) [Inhibition of platelet aggregation with 5 mcM ADP; larger value indicates greater platelet inhibition.] | 300 mg (24 h) | 24 (26) | 37 (21) | 39 (28) | 40 (21)
 | 600 mg (24 h) | 32 (25) | 56 (22) | 49 (23) | 51 (28)
 | 75 mg (Day 5) | 37 (23) | 60 (18) | 58 (19) | 56 (13)
 | 150 mg (Day 5) | 61 (14) | 74 (14) | 73 (9) | 68 (18)
VASP-PRI (%) [Vasodilator-stimulated phosphoprotein – platelet reactivity index; smaller value indicates greater platelet inhibition.] | 300 mg (24 h) | 91 (12) | 78 (12) | 68 (16) | 73 (12)
 | 600 mg (24 h) | 85 (14) | 56 (26) | 48 (20) | 51 (20)
 | 75 mg (Day 5) | 83 (13) | 50 (16) | 39 (14) | 40 (9)
 | 150 mg (Day 5) | 61 (18) | 29 (11) | 24 (10) | 20 (10)
Values are mean (SD).

13 NONCLINICAL TOXICOLOGY

13.1 Carcinogenesis, Mutagenesis, Impairment of Fertility

There was no evidence of tumorigenicity when clopidogrel was administered for 78 weeks to mice and 104 weeks to rats at dosages up to 77 mg/kg per day, which afforded plasma exposures >25 times that in humans at the recommended daily dose of 75 mg.

Clopidogrel was not genotoxic in four in vitro tests (Ames test, DNA-repair test in rat hepatocytes, gene mutation assay in Chinese hamster fibroblasts, and metaphase chromosome analysis of human lymphocytes) and in one in vivo test (micronucleus test by oral route in mice).

Clopidogrel was found to have no effect on fertility of male and female rats treated prior to pairing and throughout gestation at oral doses up to 400 mg/kg per day (52 times the recommended human dose on a mg/m^2 basis).

14 CLINICAL STUDIES

14.1 Acute Coronary Syndrome

CURE

The CURE study included 12,562 patients with ACS without ST-elevation (UA or NSTEMI) and presenting within 24 hours of onset of the most recent episode of chest pain or symptoms consistent with ischemia. Patients were required to have either ECG changes compatible with new ischemia (without ST-elevation) or elevated cardiac enzymes or troponin I or T to at least twice the upper limit of normal.

Patients were randomized to receive Plavix (300 mg loading dose followed by 75 mg once daily) or placebo, and were treated for up to one year. Patients also received aspirin (75–325 mg once daily) and other standard therapies such as heparin. The use of GPIIb/IIIa inhibitors was not permitted for three days prior to randomization.

The patient population was largely White (82%) and included 38% women, and 52% age ≥65 years of age. Only about 20% of patients underwent revascularization during the initial hospitalization and few underwent emergent or urgent revascularization.

The number of patients experiencing the primary outcome (CV death, MI, or stroke) was 582 (9.3%) in the Plavix-treated group and 719 (11.4%) in the placebo-treated group, a 20% relative risk reduction (95% CI of 10%–28%; p <0.001) for the Plavix-treated group (see Table 4).

Table 4: Outcome Events in the CURE Primary Analysis
Outcome | Plavix (+ aspirin) [Other standard therapies were used as appropriate.] | Placebo (+ aspirin) | Relative Risk Reduction (%) (95% CI)
 | (n=6259) | (n=6303)
Primary outcome (Cardiovascular death, MI, stroke) | 582 (9.3%) | 719 (11.4%) | 20% (10.3, 27.9) p <0.001
All Individual Outcome Events: [The individual components do not represent a breakdown of the primary and coprimary outcomes, but rather the total number of subjects experiencing an event during the course of the study.]
CV death | 318 (5.1%) | 345 (5.5%) | 7% (-7.7, 20.6)
MI | 324 (5.2%) | 419 (6.6%) | 23% (11.0, 33.4)
Stroke | 75 (1.2%) | 87 (1.4%) | 14% (-17.7, 36.6)

Most of the benefit of Plavix occurred in the first two months, but the difference from placebo was maintained throughout the course of the trial (up to 12 months) (see Figure 2).

Figure 2: Cardiovascular Death, Myocardial Infarction, and Stroke in the CURE Study

The effect of Plavix did not differ significantly in various subgroups, as shown in Figure 3. The benefits associated with Plavix were independent of the use of other acute and long-term cardiovascular therapies, including heparin/LMWH, intravenous glycoprotein IIb/IIIa (GPIIb/IIIa) inhibitors, lipid-lowering drugs, beta-blockers, and ACE inhibitors. The efficacy of Plavix was observed independently of the dose of aspirin (75–325 mg once daily). The use of oral anticoagulants, nonstudy antiplatelet drugs, and chronic NSAIDs was not allowed in CURE.

Figure 3: Hazard Ratio for Patient Baseline Characteristics and On-Study Concomitant Medications/Interventions for the CURE Study

The use of Plavix in CURE was associated with a decrease in the use of thrombolytic therapy (71 patients [1.1%] in the Plavix group, 126 patients [2.0%] in the placebo group; relative risk reduction of 43%), and GPIIb/IIIa inhibitors (369 patients [5.9%] in the Plavix group, 454 patients [7.2%] in the placebo group, relative risk reduction of 18%). The use of Plavix in CURE did not affect the number of patients treated with CABG or PCI (with or without stenting) (2253 patients [36.0%] in the Plavix group, 2324 patients [36.9%] in the placebo group; relative risk reduction of 4.0%).

COMMIT

In patients with STEMI, the safety and efficacy of Plavix were evaluated in the randomized, placebo-controlled, double-blind study, COMMIT. COMMIT included 45,852 patients presenting within 24 hours of the onset of the symptoms of myocardial infarction with supporting ECG abnormalities (i.e., ST-elevation, ST-depression or left bundle-branch block). Patients were randomized to receive Plavix (75 mg once daily) or placebo, in combination with aspirin (162 mg per day), for 28 days or until hospital discharge, whichever came first.

The primary endpoints were death from any cause and the first occurrence of re-infarction, stroke or death.

The patient population was 28% women and 58% age ≥60 years (26% age ≥70 years). Fifty-five percent (55%) of patients received thrombolytics and only 3% underwent PCI.

As shown in Table 5 and Figure 4 and Figure 5 below, Plavix significantly reduced the relative risk of death from any cause by 7% (p=0.029), and the relative risk of the combination of re-infarction, stroke or death by 9% (p=0.002).

Table 5: Outcome Events in COMMIT
Event | Plavix (+ aspirin) (N=22961) | Placebo (+ aspirin) (N=22891) | Odds ratio (95% CI) | p-value
Composite endpoint: Death, MI, or Stroke [9 patients (2 clopidogrel and 7 placebo) suffered both a nonfatal stroke and a nonfatal MI.] | 2121 (9.2%) | 2310 (10.1%) | 0.91 (0.86, 0.97) | 0.002
Death | 1726 (7.5%) | 1845 (8.1%) | 0.93 (0.87, 0.99) | 0.029
Nonfatal MI [Nonfatal MI and nonfatal stroke exclude patients who died (of any cause).] | 270 (1.2%) | 330 (1.4%) | 0.81 (0.69, 0.95) | 0.011
Nonfatal Stroke | 127 (0.6%) | 142 (0.6%) | 0.89 (0.70, 1.13) | 0.33

Figure 4: Cumulative Event Rates for Death in the COMMIT Study [All treated patients received aspirin.]

Figure 5: Cumulative Event Rates for the Combined Endpoint Re-Infarction, Stroke or Death in the COMMIT Study [All treated patients received aspirin.]

The effect of Plavix did not differ significantly in various prespecified subgroups as shown in Figure 6. The effect was also similar in non-prespecified subgroups including those based on infarct location, Killip class or prior MI history. Such subgroup analyses should be interpreted cautiously.

Figure 6: Effects of Adding Plavix to Aspirin on the Combined Primary Endpoint across Baseline and Concomitant Medication Subgroups for the COMMIT Study

* CI is 95% for Overall row only.

14.2 Recent Myocardial Infarction, Recent Stroke, or Established Peripheral Arterial Disease

CAPRIE

The CAPRIE trial was a 19,185-patient, 304-center, international, randomized, double-blind, parallel-group study comparing Plavix (75 mg daily) to aspirin (325 mg daily). To be eligible to enroll, patients had to have: 1) recent history of myocardial infarction (within 35 days); 2) recent histories of ischemic stroke (within 6 months) with at least a week of residual neurological signs; and/or 3) established peripheral arterial disease (PAD). Patients received randomized treatment for an average of 1.6 years (maximum of 3 years).

The trial's primary outcome was the time to first occurrence of new ischemic stroke (fatal or not), new myocardial infarction (fatal or not), or other vascular death. Deaths not easily attributable to nonvascular causes were all classified as vascular.

Table 6: Outcome Events in the CAPRIE Primary Analysis
Patients | Plavix n=9599 | Aspirin n=9586
Ischemic stroke (fatal or not) | 438 (4.6%) | 461 (4.8%)
MI (fatal or not) | 275 (2.9%) | 333 (3.5%)
Other vascular death | 226 (2.4%) | 226 (2.4%)
Total | 939 (9.8%) | 1020 (10.6%)

As shown in Table 6, Plavix was associated with a lower incidence of outcome events, primarily MI. The overall relative risk reduction (9.8% vs 10.6%) was 8.7%, p=0.045. Similar results were obtained when all-cause mortality and all-cause strokes were counted instead of vascular mortality and ischemic strokes (risk reduction 6.9%). In patients who survived an on-study stroke or myocardial infarction, the incidence of subsequent events was lower in the Plavix group.

The curves showing the overall event rate are shown in Figure 7. The event curves separated early and continued to diverge over the 3-year follow-up period.

Figure 7: Fatal or Nonfatal Vascular Events in the CAPRIE Study

The statistical significance favoring Plavix over aspirin was marginal (p=0.045). However, because aspirin is itself effective in reducing cardiovascular events in patients with recent myocardial infarction or stroke, the effect of Plavix is substantial.

The CAPRIE trial enrolled a population that had recent MI, recent stroke, or PAD. The efficacy of Plavix relative to aspirin was heterogeneous across these subgroups (p=0.043) (see Figure 8). Nonetheless, this difference may be a chance occurrence because the CAPRIE trial was not designed to evaluate the relative benefit of Plavix over aspirin in the individual patient subgroups. The benefit was most apparent in patients who were enrolled because of peripheral arterial disease and less apparent in stroke patients. In patients who were enrolled in the trial on the sole basis of a recent myocardial infarction, Plavix was not numerically superior to aspirin.

Figure 8: Hazard Ratio and 95% CI by Baseline Subgroups in the CAPRIE Study

14.3 No Demonstrated Benefit of Plavix plus Aspirin in Patients with Multiple Risk Factors or Established Vascular Disease

CHARISMA

The CHARISMA trial was a 15,603 subject, randomized, double-blind, parallel group study comparing Plavix (75 mg daily) to placebo for prevention of ischemic events in patients with vascular disease or multiple risk factors for atherosclerosis. All subjects were treated with aspirin 75–162 mg daily. The mean duration of treatment was 23 months. The study failed to demonstrate a reduction in the occurrence of the primary endpoint, a composite of CV death, MI, or stroke. A total of 534 (6.9%) patients in the Plavix group versus 573 (7.4%) patients in the placebo group experienced a primary outcome event (p=0.22). Bleeding of all severities was more common in the subjects randomized to Plavix.

16 HOW SUPPLIED/STORAGE AND HANDLING

Plavix (clopidogrel tablets) 75 mg are available as pink, round, biconvex, film-coated tablets debossed with "75" on one side and "1171" on the other. Tablets are provided as follows:

NDC 0024-1171-90 | Bottles of 90

Plavix (clopidogrel tablets) 300 mg are available as pink, oblong, film-coated tablets debossed with "300" on one side and "1332" on the other. Tablets are provided as follows:

NDC 0024-1332-30 | Unit-dose packages of 30

STORAGE AND HANDLING

Store at 25°C (77°F); excursions permitted to 15°C–30°C (59°F–86°F) [see USP Controlled Room Temperature].

17 PATIENT COUNSELING INFORMATION

Advise patients to read FDA approved patient labeling (Medication Guide).

Discontinuation

Advise patients not to discontinue Plavix without first discussing it with the healthcare provider who prescribed it [see Warnings and Precautions (5.3)].

Bleeding

Advise patients that they:

- will bruise and bleed more easily
- will take longer than usual to stop bleeding
- must report any unanticipated, prolonged, or excessive bleeding, or blood in their stool or urine [see Warnings and Precautions (5.2)]

Thrombotic Thrombocytopenic Purpura

Instruct patients to get prompt medical attention if they experience symptoms of TTP that cannot otherwise be explained [see Warnings and Precautions (5.4)].

Invasive Procedures

Advise patients to inform physicians and dentists that they are taking Plavix before any surgery or dental procedure [see Warnings and Precautions (5.2, 5.3)].

Proton Pump Inhibitors

Advise patients not to take omeprazole or esomeprazole while taking Plavix. Dexlansoprazole, lansoprazole, and pantoprazole had less pronounced effects on the antiplatelet activity of Plavix than did omeprazole or esomeprazole [see Drug Interactions (7.1)].

Manufactured by:
sanofi-aventis U.S. LLC
Morristown, NJ 07960
A SANOFI COMPANY

Medication Guide
Plavix® (PLAV-iks)
(clopidogrel tablets)

Read this Medication Guide before you start taking Plavix and each time you get a refill. There may be new information. This Medication Guide does not take the place of talking with your doctor about your medical condition or your treatment.

What is the most important information I should know about Plavix?

1. Plavix may not work as well in people who:
  - have certain genetic factors that affect how the body breaks down Plavix. Your doctor may do genetic tests to make sure Plavix is right for you.
  - take certain medicines, especially omeprazole (Prilosec®) or esomeprazole (Nexium®). Your doctor may change the medicine you take for stomach acid problems while you take Plavix.
2. Plavix can cause bleeding which can be serious and can sometimes lead to death. Plavix is a blood thinner medicine that lowers the chance of blood clots forming in your body. While you take Plavix:
  - you may bruise and bleed more easily
  - you are more likely to have nose bleeds
  - it will take longer for any bleeding to stop

Call your doctor right away if you have any of these signs or symptoms of bleeding:

- unexpected bleeding or bleeding that lasts a long time
- blood in your urine (pink, red or brown urine)
- red or black stools (looks like tar)
- bruises that happen without a known cause or get larger
- cough up blood or blood clots
- vomit blood or your vomit looks like coffee grounds

Do not stop taking Plavix without talking to the doctor who prescribes it for you. People who stop taking Plavix too soon have a higher risk of having a heart attack or dying. If you must stop Plavix because of bleeding, your risk of a heart attack may be higher.

What is Plavix?

Plavix is a prescription medicine used to treat people who have any of the following:

- chest pain due to heart problems
- poor circulation in their legs (peripheral arterial disease)
- a heart attack
- a stroke

Plavix is used alone or with aspirin to lower your chance of having another serious problem with your heart or blood vessels such as heart attack, stroke, or blood clot that can lead to death.

Platelets are blood cells that help your blood clot normally. Plavix helps to prevent platelets from sticking together and forming a clot that can block an artery.

It is not known if Plavix is safe and effective in children.

Who should not take Plavix?

Do not take Plavix if you:

- currently have a condition that causes bleeding, such as a stomach ulcer
- are allergic to clopidogrel or other ingredients in Plavix. See the end of this leaflet for a complete list of ingredients in Plavix.

What should I tell my doctor before taking Plavix?

Before you take Plavix, tell your doctor if you:

- have a history of bowel (gastrointestinal) or stomach ulcers.
- have a history of bleeding problems.
- plan to have surgery or a dental procedure. See "How should I take Plavix?"
- are pregnant or plan to become pregnant. It is not known if Plavix will harm your unborn baby.
- are breastfeeding or plan to breastfeed. It is not known if Plavix passes into your breast milk. A decision should be made with your healthcare provider to avoid or discontinue breastfeeding when continuing Plavix is needed.
- have had an allergy or reaction to any medicine used to treat your disease.

Tell all of your doctors and your dentist that you are taking Plavix. They should talk to the doctor who prescribed Plavix for you before you have any surgery or invasive procedure.

Tell your doctor about all the medicines you take, including prescription, non-prescription medicines, vitamins and herbal supplements.

Plavix may affect the way other medicines work, and other medicines may affect how Plavix works. See "What is the most important information I should know about Plavix?"

Plavix may increase blood levels of other medicines such as repaglinide (Prandin®).

Taking Plavix with certain other medicines may increase your risk of bleeding. Especially tell your doctor if you take:

- aspirin, especially if you have had a stroke. Always talk to your doctor about whether you should take aspirin along with Plavix to treat your condition.
- nonsteroidal anti-inflammatory drugs (NSAIDs). Ask your doctor or pharmacist for a list of NSAID medicines if you are not sure.
- warfarin (Coumadin®, Jantoven®).
- selective serotonin reuptake inhibitors (SSRIs) and serotonin norepinephrine reuptake inhibitors (SNRIs). Ask your doctor or pharmacist for a list of SSRI or SNRI medicines if you are not sure.
- rifampin (used to treat severe infections)
- other antiplatelet agents

Know the medicines you take. Keep a list of them to show your doctor or pharmacist when you get a new medicine.

How should I take Plavix?

- Take Plavix exactly as your doctor tells you.
- Do not change your dose or stop taking Plavix without talking to your doctor first. Stopping Plavix may increase your risk of heart attack or stroke.
- Take Plavix with aspirin as instructed by your doctor.
- If you miss a dose, take Plavix as soon as you remember. If it is almost time for your next dose, skip the missed dose. Take the next dose at your regular time. Do not take 2 doses of Plavix at the same time unless your doctor tells you to.
- If you take too much Plavix, call your doctor or go to the nearest emergency room right away.
- Talk with your doctor about stopping your Plavix before you have surgery. Your doctor may tell you to stop taking Plavix at least 5 days before you have surgery to avoid excessive bleeding during surgery.

What are the possible side effects of Plavix?

Plavix can cause serious side effects including:

- See "What is the most important information I should know about Plavix?"
- A blood clotting problem called Thrombotic Thrombocytopenic Purpura (TTP). TTP can happen with Plavix, sometimes after a short time (less than 2 weeks). TTP is a blood clotting problem where blood clots form in blood vessels; and can happen anywhere in the body. TTP needs to be treated in a hospital right away because it may cause death. Get medical help right away if you have any of these symptoms and they cannot be explained by another medical condition:
  - purplish spots (called purpura) on the skin or in the mouth (mucous membranes) due to bleeding under the skin
  - your skin or the whites of your eyes are yellow (jaundice)
  - you feel tired or weak
  - your skin looks very pale
  - fever
  - fast heart rate or feeling short of breath
  - headache
  - speech changes
  - confusion
  - coma
  - stroke
  - seizure
  - low amount of urine, or urine that is pink or has blood in it
  - stomach area (abdominal) pain
  - nausea, vomiting, or diarrhea
  - vision changes
  - persistent low blood sugar symptoms

Tell your doctor if you have any side effect that bothers you or that does not go away. Tell your doctor if you develop an allergic reaction including skin reactions while taking Plavix.

These are not all the possible side effects of Plavix. For more information, ask your doctor or pharmacist.

Call your doctor for medical advice about side effects. You may report side effects to FDA at 1-800-FDA-1088.

How should I store Plavix?

- Store Plavix at 59°F to 86°F (15°C to 30°C).

Keep Plavix and all medicines out of the reach of children.

General information about Plavix

Medicines are sometimes used for purposes other than those listed in a Medication Guide. Do not take Plavix for a condition for which it was not prescribed. Do not give Plavix to other people, even if they have the same symptoms that you have. It may harm them.

This Medication Guide summarizes the most important information about Plavix. If you would like more information, talk to your doctor. Ask your doctor or pharmacist for information about Plavix that was written for healthcare professionals.

For more information, go to www.sanofi-aventis.us or call 1-800-633-1610.

What are the ingredients in Plavix?

Active ingredient: clopidogrel bisulfate

Inactive ingredients:

Tablet: hydrogenated castor oil, hydroxypropyl cellulose, mannitol, microcrystalline cellulose, polyethylene glycol 6000

Film coating: ferric oxide, hypromellose 2910, lactose monohydrate, titanium dioxide, triacetin, Carnauba wax

This Medication Guide has been approved by the U.S. Food and Drug Administration.

Revised: May 2025

Manufactured by:
sanofi-aventis U.S. LLC
Morristown, NJ 07960
A SANOFI COMPANY

Plavix® is a registered trademark of sanofi-aventis.
All other trademarks are property of their respective owners.

PRINCIPAL DISPLAY PANEL - 75 mg Tablet Bottle Label

NDC 0024-1171-90
Rx only

Plavix®
(clopidogrel tablets)

75 mg

Dispense with
Medication Guide

90 Tablets
SANOFI

PRINCIPAL DISPLAY PANEL - 300 mg Tablet Blister Pack Carton

NDC 0024-1332-30
Rx only

Plavix®
(clopidogrel tablets)
300 mg
Dispense with Medication Guide

30 film-coated tablets
SANOFI